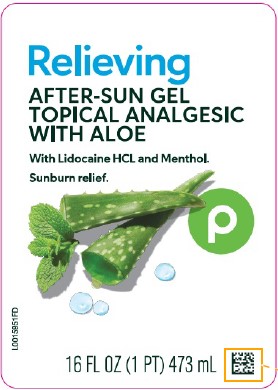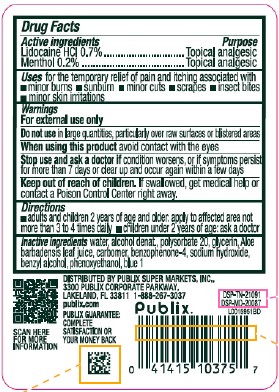 DRUG LABEL: Aloe Vera Gel
NDC: 56062-747 | Form: GEL
Manufacturer: Publix Super Markets, Inc.
Category: otc | Type: HUMAN OTC DRUG LABEL
Date: 20260205

ACTIVE INGREDIENTS: LIDOCAINE HYDROCHLORIDE 7 mg/1 mL; MENTHOL 2 mg/1 mL
INACTIVE INGREDIENTS: WATER; ALCOHOL; POLYSORBATE 20; GLYCERIN; ALOE VERA LEAF; CARBOMER HOMOPOLYMER, UNSPECIFIED TYPE; SULISOBENZONE; SODIUM HYDROXIDE; BENZYL ALCOHOL; PHENOXYETHANOL; FD&C BLUE NO. 1

Publix 747.002/747AC
After Sun Gel with Aloe

Active ingredient

Lidocaine HCl 0.7%

Menthol 0.2%

Purpose

Topical analgesic

Uses

for the temporary relief of pain and itching associated with

- minor burns
- sunburn
- minor cuts
- scrapes
- insect bites
- minor skin irritations

Warnings

For external use only

Do not use

in large quantities, particularly over raw surfaces or blistered areas

when using this product

avoid contact with the eyes

Stop use and ask a doctor if

condition worsens, or if symptoms persist for more than 7 days or clear up and occur again within a few days

Keep out of reach of children.

If swallowed, get medical help or contact a Poison Control Center right away.

Directions

- adults and children 2 years of age and older: apply to affected area not more than 3 to 4 times daily
- children under 2 years of age: ask a doctor

Inactive ingredients

water, alcohol denat., polysorbate 20, glycerin, Aloe barbadensis leaf juice, carbomer, benzophenone-4, sodium hydroxide, benzyl alcohol, phenoxyethanol, blue 1

ADVERSE REACTION

DISTRIBUTED BY PUBLIX SUPER MARKETS, INC.,

3300 PUBLIX CORPORATE PARKWAY,

LAKELAND, FL 33811 1-888-267-3037

publix.com

PUBLIX GUARANTEE: COMPLETE SATISFACTION OR YOUR MONEY BACK

SCAN HERE FOR MORE INFORMATION

DSP-TN-21091

DSP-MP-20087

principal display panel

Relieving

AFTER-SUN GEL

TOPICAL ANALGESIC

WITH ALOE

WITH LIDOCAINE HCL AND MENTHOL.

SUNBURN RELIEF.

P

16 FL OZ (1 PT) 473 mL